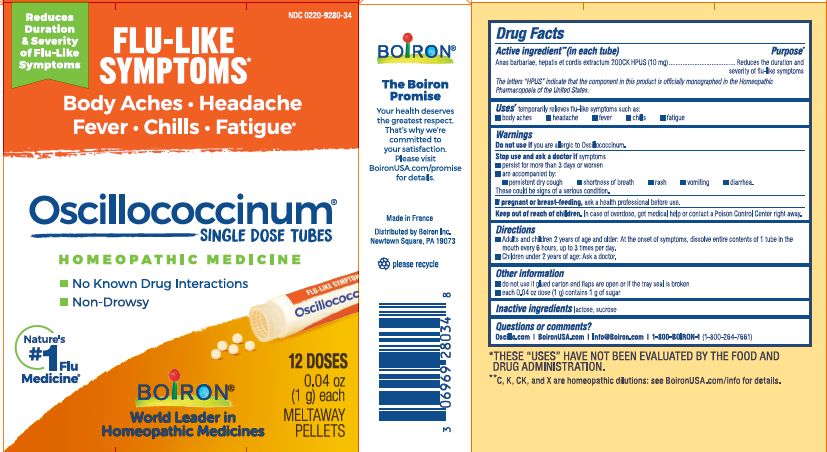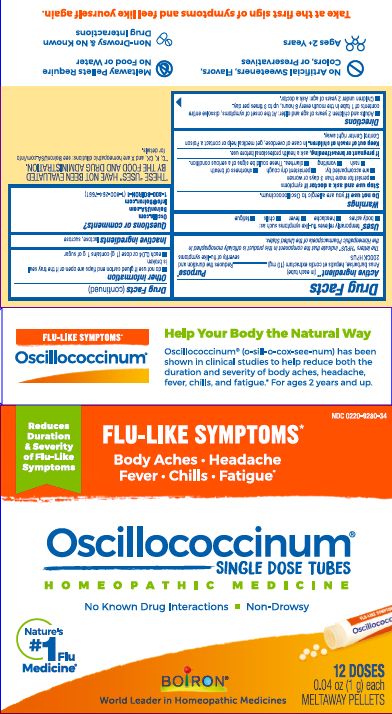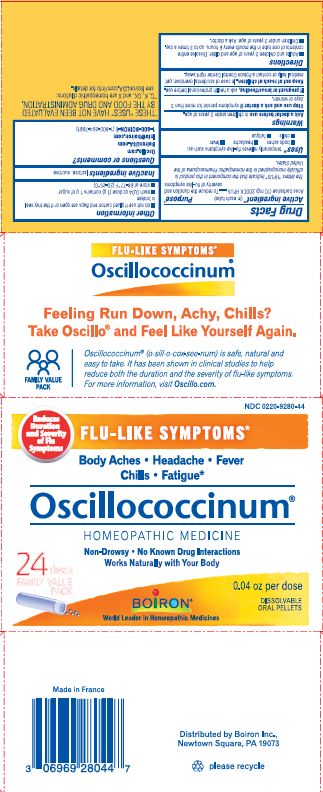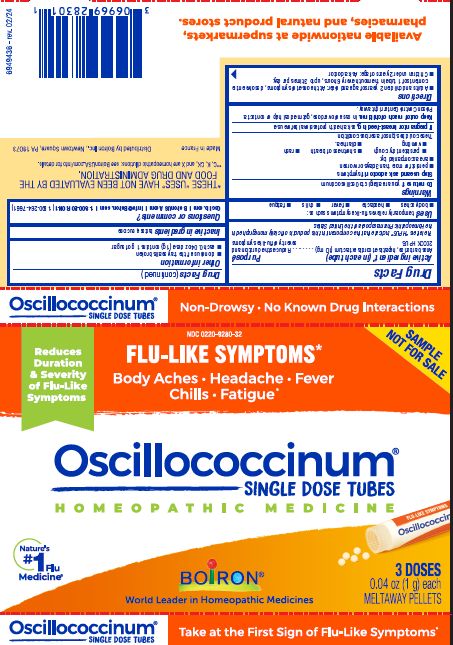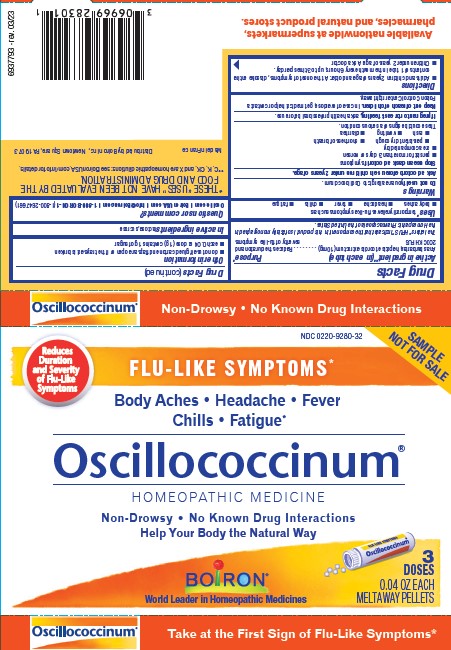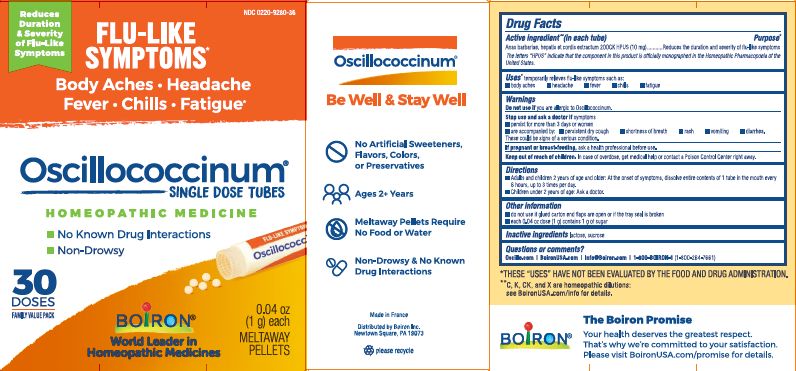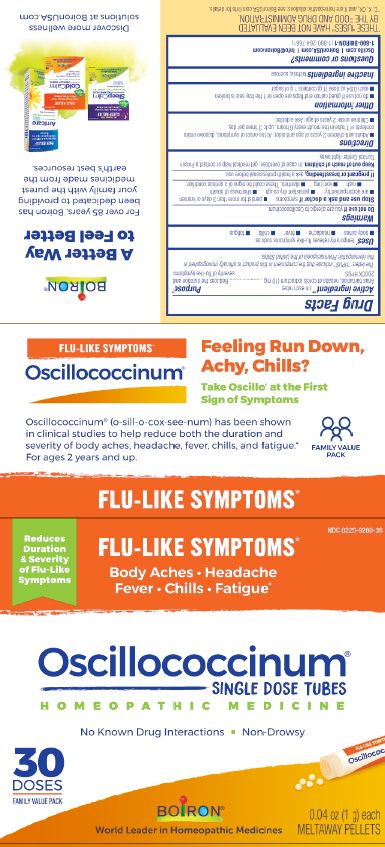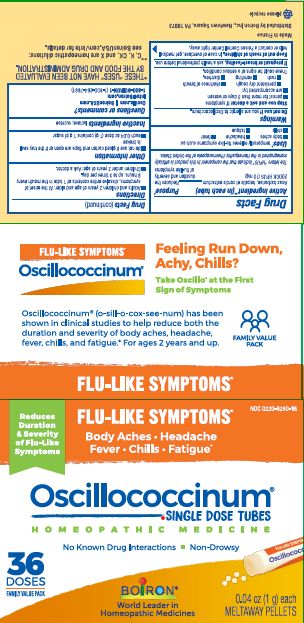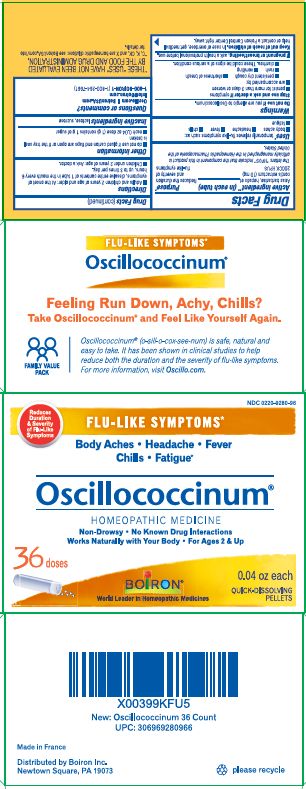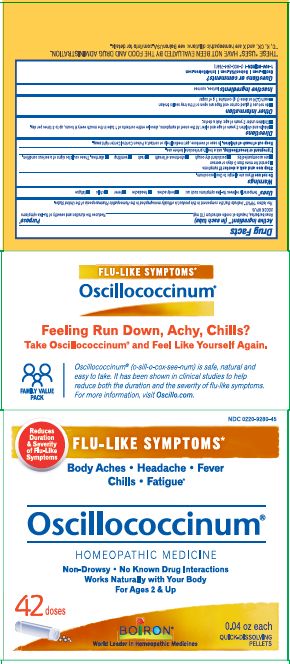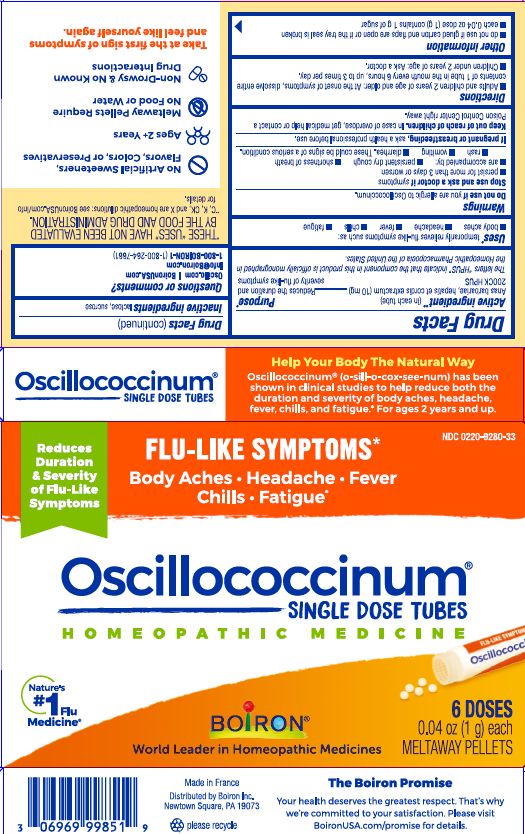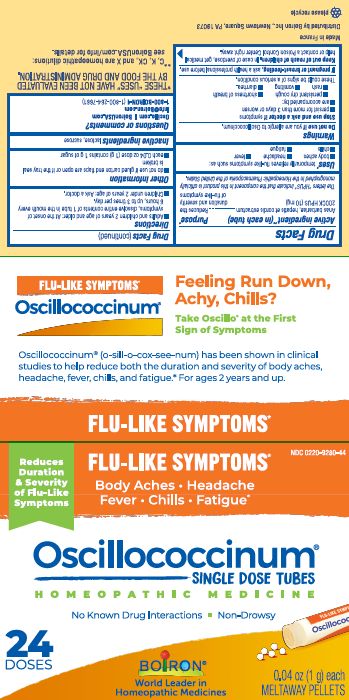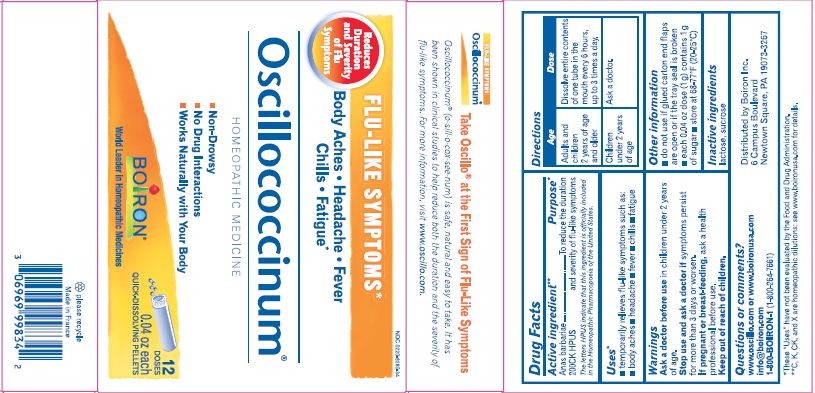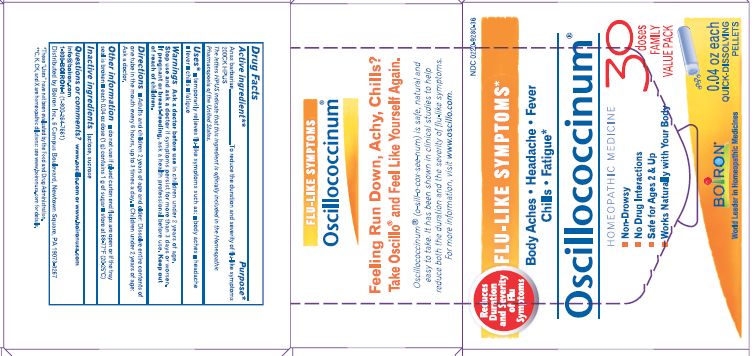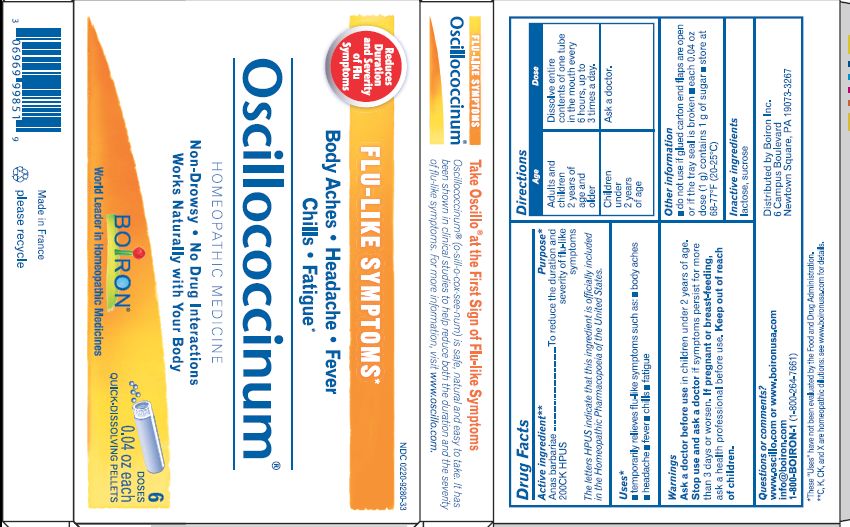 DRUG LABEL: Oscillococcinum
NDC: 0220-9280 | Form: PELLET
Manufacturer: Laboratoires Boiron
Category: homeopathic | Type: HUMAN OTC DRUG LABEL
Date: 20240731

ACTIVE INGREDIENTS: CAIRINA MOSCHATA HEART/LIVER AUTOLYSATE 200 [hp_C]/1 1
INACTIVE INGREDIENTS: LACTOSE; SUCROSE

Oscillococcinum

Active Ingredient** (in each tube)

Anas barbariae, hepatis et cordis extractum (10 mg) 200CK HPUS

The letters "HPUS" indicate that the components in this product are officially monographed in the Homeopathic Pharmacopoeia of the United States.

Purpose*

Anas barbariae, hepatis et cordis extractum 200CK HPUS ..... Reduces the duration and severity of flu-like symptoms

Uses*

temporarily relieves flu-like symptoms such as:

- body aches
- headache
- fever
- chills
- fatigue

Do not use if you are allergic to Oscillococcinum.

Stop use and ask a doctor if symptoms

- persist for more than 3 days or worsen
- are accompanied by:
- persistent dry cough
- shortness of breath
- rash
- vomiting
- diarrhea.

These could be signs of a serious condition.

PREGNANCY OR BREAST FEEDING

If pregnant or breast-feeding, ask a health professional before use.

Keep out of reach of children. In case of overdose, get medical help or contact a Poison Control Center right away.

DOSAGE AND ADMINISTRATION

- Adults and children 2 years of age and older: At the onset of symptoms, dissolve entire contents of 1 tube in the mouth every 6 hours, up to 3 times per day.
- Children under 2 years of age: Ask a doctor.

INACTIVE INGREDIENT

lactose, sucrose.

do not use if glued carton end flaps are open or if the tray seal is broken

each 0.04 oz dose (1g) contains 1g of sugar

0.04 oz (1 g) each

Meltaway Pellets

Body Aches, Headache, Fever, Chills, Fatigue*

Flu-like Symptoms*

Non-Drowsy No Known Drug Interactions

Works Naturally with your Body

3 Dose

6 Dose
12 Dose
24 Dose
30 Dose

36 Dose
42 Dose

*THESE “USES” HAVE NOT BEEN EVALUATED BY THE FOOD AND DRUG ADMINISTRATION.

*C,K,CK, and X are homeopathic dilutions: see BoironUSA.com/info for details.

Questions, comments?

Oscillo.com
BoironUSA.com
Info@boironusa.com
1-800-BOIRON-1 (1-800-264-7661)
Distributed by Boiron Inc.
Newtown Square, PA 19073